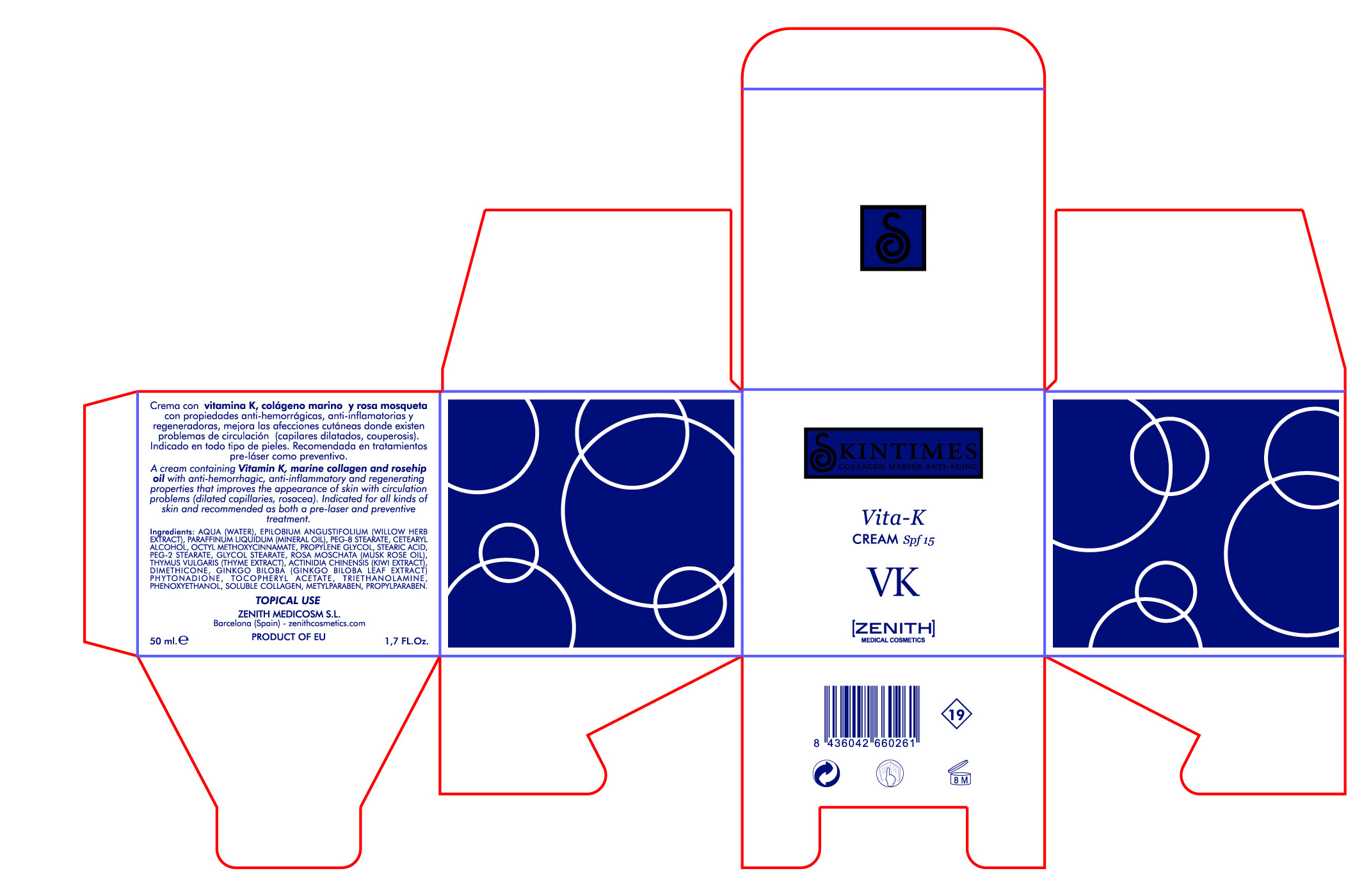 DRUG LABEL: Vita
NDC: 42248-103 | Form: CREAM
Manufacturer: Zenith Medicosm SL
Category: otc | Type: HUMAN OTC DRUG LABEL
Date: 20120121

ACTIVE INGREDIENTS: OCTINOXATE 3.75 mL/50 mL
INACTIVE INGREDIENTS: PEG-2 STEARATE; PROPYLPARABEN; ALPHA-TOCOPHEROL ACETATE; DIMETHICONE; GLYCOL STEARATE; ROSA MOSCHATA OIL; WATER; MINERAL OIL; CETOSTEARYL ALCOHOL; PEG-8 STEARATE; TROLAMINE; THYME; KIWI FRUIT; PHYTONADIONE; METHYLPARABEN; COLLAGEN, SOLUBLE, FISH SKIN; STEARIC ACID; PROPYLENE GLYCOL; EPILOBIUM ANGUSTIFOLIUM LEAF; GINKGO; PHENOXYETHANOL

Drug Facts

Active Ingredient

Octinoxate 7.5%

Description

A cream containing Vitamin K, marine collagen, rosehip oil with anti-hemorrhagic,anti-inflammatory and regenerating properties that improves the appearance of skin with circulation problems (dilated capillaries, rosacea). Indicated for all kinds of skin and recommended as both a pre-laser and preventive treatment.

50ml. 1.7 fl. Oz

Warning

TOPICAL USE